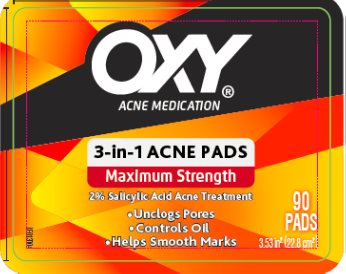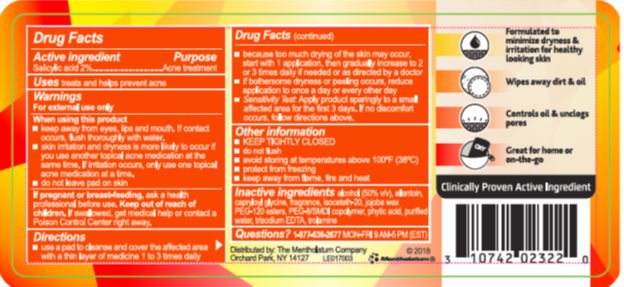 DRUG LABEL: OXY 3 in 1 Acne Pads
NDC: 10742-4359 | Form: SWAB
Manufacturer: The Mentholatum Company
Category: otc | Type: HUMAN OTC DRUG LABEL
Date: 20241217

ACTIVE INGREDIENTS: SALICYLIC ACID 20 mg/1 1
INACTIVE INGREDIENTS: ALCOHOL; ALLANTOIN; CAPRYLOYL GLYCINE; ISOCETETH-20; ETHYL JOJOBATE; PEG-8/SMDI COPOLYMER; FYTIC ACID; WATER; EDETATE TRISODIUM; TROLAMINE

Drug Facts

Active ingredient

Salicylic acid 2%

Purpose

Salicylic acid - Acne treatment

Uses

treats and helps prevent acne

Warnings

For external use only

When using this product

- keep away from eyes, lips and mouth. If contact occurs, flush thoroughly with water.
- skin irritation and dryness is more likely to occur if you use another topical acne medication at the same time. If irritation occurs, only use one topical acne medication at a time.
- do not leave pad on skin

If pregnant or breast-feeding

ask a health professional before use.

Keep out of reach of children.

If swallowed, get medical help or contact a Poison Control Center right away.

Directions

- use a pad to cleanse and cover the affected area with a thin layer of medicine 1 to 3 times daily
- because too much drying of the skin may occur, start with 1 application, then gradually increase to 2 or 3 times daily if needed or as directed by a doctor
- if bothersome dryness or peeling occurs, reduce application to once a day or every other day
- Sensitivity test: Apply product sparingly to a small affected area for the first 3 days. If no discomfort occurs, follow directions above.

Other information

- KEEP TIGHTLY CLOSED
- avoid storing at temperatures above 100˚F (38˚C)
- protect from freezing
- keep away from flame, fire and heat

Inactive ingredients

alcohol (50% v/v), allantoin, capryloyl glycine, fragrance, isoceteth-20, jojoba wax PEG-120 esters, PEG-8/SMDI copolymer, phytic acid, purified water, trisodium EDTA, trolamine

Questions?

1-877-636-2677 MON-FRI 9 AM - 5 PM (EST)